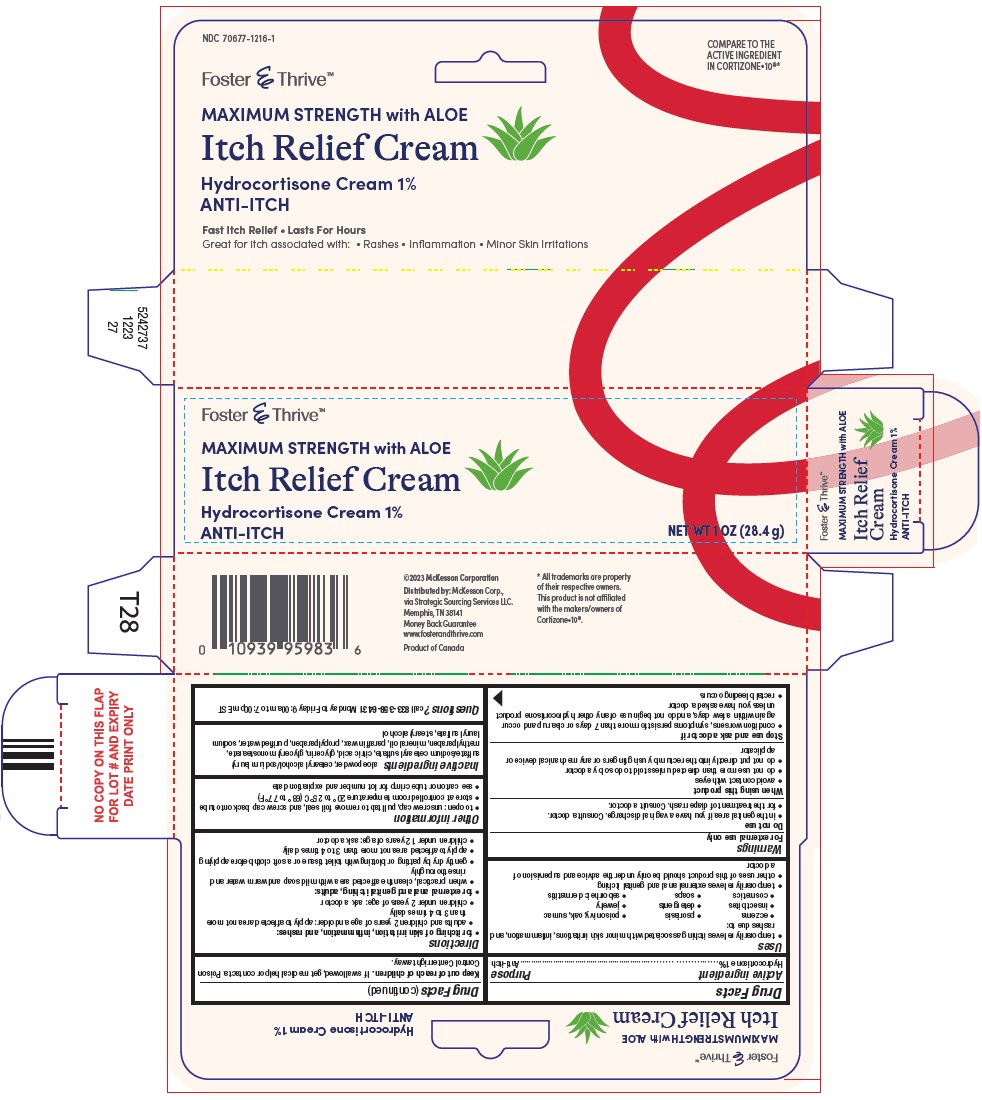 DRUG LABEL: Hydrocortisone
NDC: 70677-1216 | Form: CREAM
Manufacturer: STRATEGIC SOURCING SERVICES LLC
Category: otc | Type: HUMAN OTC DRUG LABEL
Date: 20260127

ACTIVE INGREDIENTS: HYDROCORTISONE 1 g/100 g
INACTIVE INGREDIENTS: CETOSTEARYL ALCOHOL; SODIUM CETOSTEARYL SULFATE; SODIUM LAURYL SULFATE; CITRIC ACID MONOHYDRATE; GLYCERIN; GLYCERYL MONOSTEARATE; METHYLPARABEN; MINERAL OIL; PARAFFIN; PROPYLPARABEN; WATER; STEARYL ALCOHOL

Hydrocortisone 1% with Aloe

Drug Facts

Active ingredient

Hydrocortisone 1%

Purpose

Anti-itch

Uses

- temporarily relieves itching associated with minor skin irritations, inflammation, and rashes due to:
  - eczema
  - psoriasis
  - poison ivy, oak, sumac
  - insect bites
  - detergents
  - jewelry
  - cosmetics
  - soaps
  - seborrheic dermatitis
- temporarily relieves external anal and genital itching
- other uses of this product should be only under the advice and supervision of a doctor

Warnings

For external use only

Do not use

- in the genital area if you have a vaginal discharge. Consult a doctor.
- for the treatment of diaper rash. Consult a doctor.

When using this product

- avoid contact with eyes
- do not use more than directed unless told to do so by a doctor
- do not put directly into the rectum by using fingers or any mechanical device or applicator

Stop use and ask a doctor if

- condition worsens, symptoms persist for more than 7 days or clear up and occur again within a few days, and do not begin use of any other hydrocortisone product unless you have asked a doctor
- rectal bleeding occurs

Keep out of reach of children.If swallowed, get medical help or contact a Poison Control Center right away.

Directions

- for itching of skin irritation, inflammation, and rashes:
  - adults and children 2 years of age and older: apply to affected area not more than 3 to 4 times daily
  - children under 2 years of age: ask a doctor
- for external anal and genital itching, adults:
  - when practical, clean the affected area with mild soap and warm water and rinse thoroughly
  - gently dry by patting or blotting with toilet tissue or a soft cloth before applying
  - apply to affected area not more than 3 to 4 times daily
  - children under 12 years of age: ask a doctor

Other information

- to open: unscrew cap, pull tab to remove foil seal, and screw cap back onto tube
- store at controlled room temperature 20° to 25°C (68° to 77°F)
- see carton or tube crimp for lot number and expiration date

Inactive ingredients

aloe powder, cetearyl alcohol/sodium lauryl sulfate/sodium cetearyl sulfate, citric acid, glycerin, glyceryl monostearate, methylparaben, mineral oil, paraffin wax, propylparaben, purified water, sodium lauryl sulfate, stearyl alcohol

Questions?

call 833-358-6431Monday to Friday 9:00am to 7:00pm EST

Distributed by:McKesson Corp.,
via Strategic Sourcing Services LLC.
Memphis, TN 38141

PRINCIPAL DISPLAY PANEL - 28.4 g Tube Carton

Foster & Thrive ™

MAXIMUM STRENGTH with ALOE

Itch Relief Cream

Hydrocortisone Cream 1%
ANTI-ITCH

NET WT 1 OZ (28.4 g)